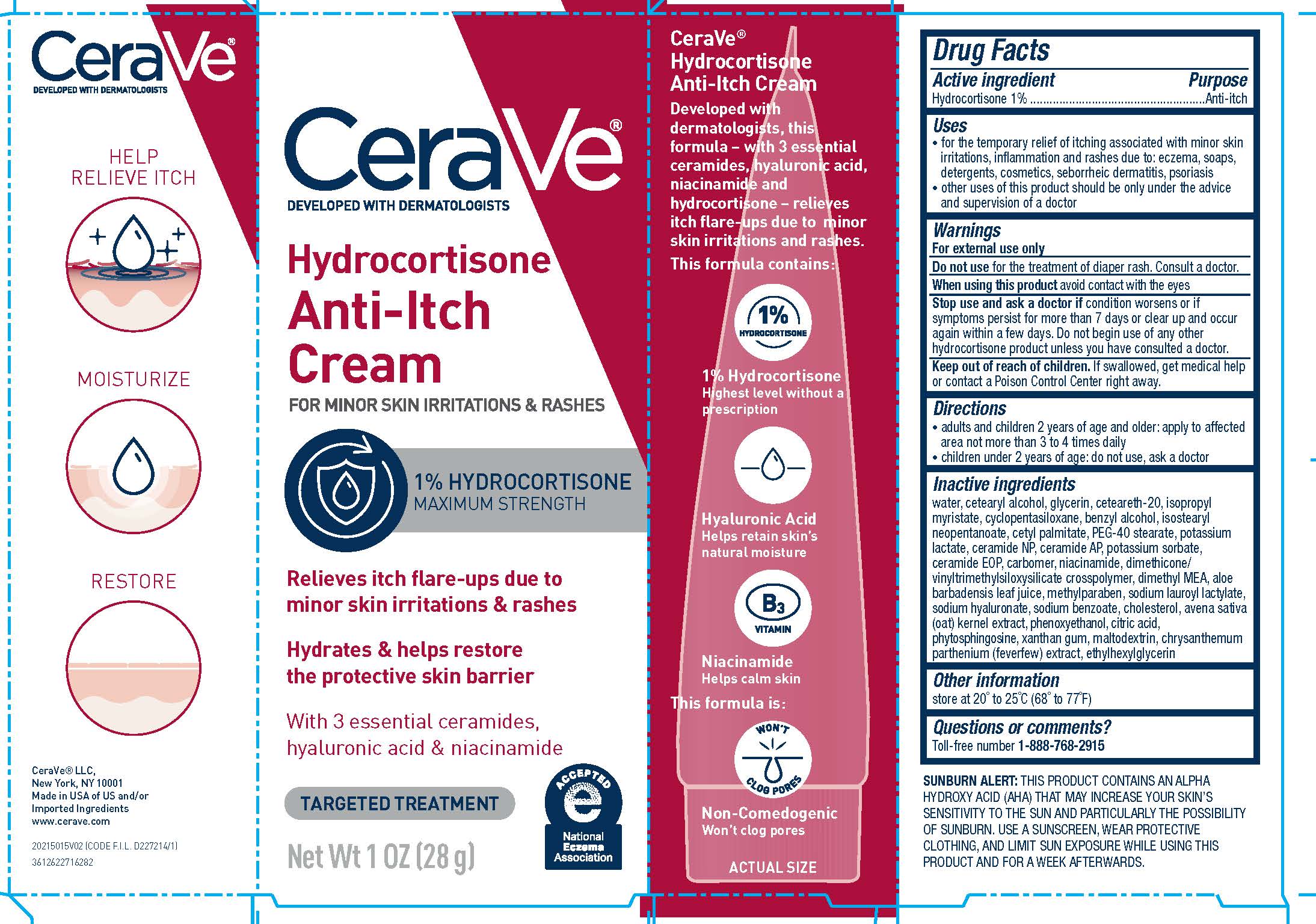 DRUG LABEL: CeraVe Developed with Dermatologists Anti Itch
NDC: 49967-108 | Form: CREAM
Manufacturer: L'Oreal USA Products Inc.
Category: otc | Type: HUMAN OTC DRUG LABEL
Date: 20231231

ACTIVE INGREDIENTS: HYDROCORTISONE 10 mg/1 g
INACTIVE INGREDIENTS: WATER; CETOSTEARYL ALCOHOL; POLYOXYL 20 CETOSTEARYL ETHER; GLYCERIN; ISOPROPYL MYRISTATE; CYCLOMETHICONE 5; BENZYL ALCOHOL; CETYL PALMITATE; ISOSTEARYL NEOPENTANOATE; CITRIC ACID MONOHYDRATE; POTASSIUM LACTATE; POTASSIUM SORBATE; DEANOL; PEG-40 STEARATE; METHYLPARABEN; ALOE VERA LEAF; NIACINAMIDE; OAT; SODIUM LAUROYL LACTYLATE; HYALURONATE SODIUM; SODIUM BENZOATE; PHENOXYETHANOL; TANACETUM PARTHENIUM; CERAMIDE 3; CERAMIDE 6 II; PHYTOSPHINGOSINE; CHOLESTEROL; XANTHAN GUM; MALTODEXTRIN; CERAMIDE 1; ETHYLHEXYLGLYCERIN

Drug Facts

Active ingredient

Hydrocortisone 1%

Purpose

Anti-itch

Uses

- temporarily relieves itching associated with minor skin irritations, inflammation, and rashes due to: eczema, soaps, detergents, cosmetics, seborrheic dermatitis, psoriasis
- other uses of this product should only be under the advice and supervision of a doctor

Warnings

For external use only

Do not uses

for the treatment of diaper rash. Consult a doctor.

When using this product

avoid contact with the eyes

Stop use and ask a doctor if

if condition worsens or if symptoms persist for more than 7 days, or clear up and occur again within a few days. Do not begin use of any other hydrocortisone product unless you have consulted a doctor.

Keep out of reach of children.

If swallowed, get medical help or contact a Poison Control Center right away.

Directions

- adults and children 2 years of age and older: apply to affected area not more than 3 to 4 times daily
- children under 2 years of age: do not use, ask a doctor

Inactive ingredients

water, cetearyl alcohol, glycerin, ceteareth-20, isopropyl myristate, cyclopentasiloxane, benzyl alcohol, isostearyl neopentanoate, cetyl palmitate, PEG-40 stearate,. potassium lactate, ceramide NP, ceramide AP, potassium sorbate,. ceramide EOP, carbomer, niacinamide, dimethicone/vinyltrimethylsiloxysilicate crosspolymer, dimethyl MEA, aloe barbadensis leaf juice, methylparaben, sodium lauroyl lactylate, sodium hyaluronate, sodium benzoate, cholesterol, avena sativa (oat) kernel extract, phenoxyethanol, citric acid, phytosphingosine, xanthan gum, maltodextrin, chrysanthemum parthenium (feverfew) extract, ethylhexylglycerin

Other information

store at 20° to 25°C (68° to 77°F)

Questions

Toll-free number 1-888-768-2915

www.CeraVe.com